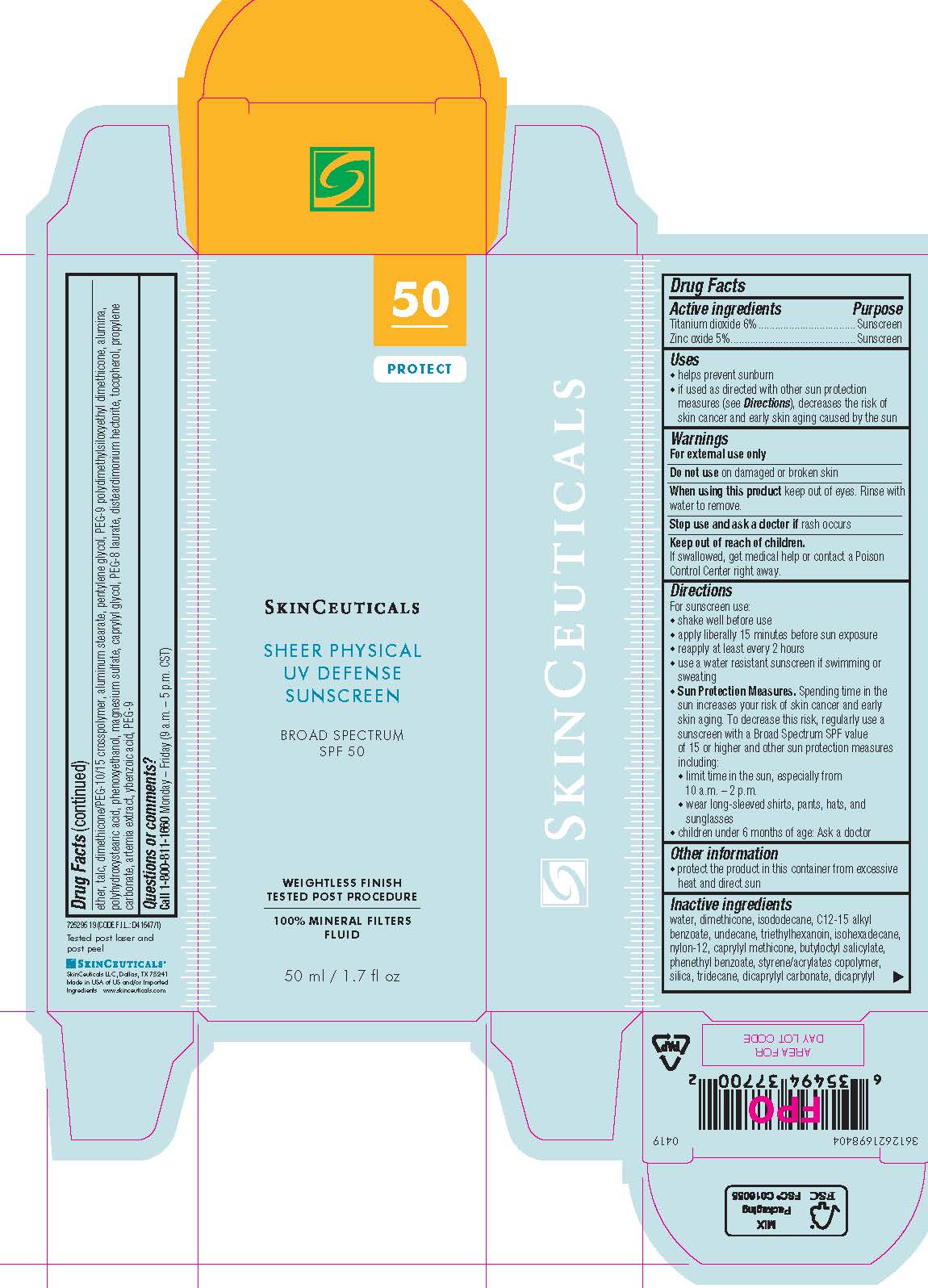 DRUG LABEL: SkinCeuticals Sheer Physical UV Defense Broad Spectrum SPF 50 Sunscreen
NDC: 49967-770 | Form: LOTION
Manufacturer: L'Oreal USA Products Inc
Category: otc | Type: HUMAN OTC DRUG LABEL
Date: 20241230

ACTIVE INGREDIENTS: TITANIUM DIOXIDE 60 mg/1 mL; ZINC OXIDE 50 mg/1 mL
INACTIVE INGREDIENTS: WATER; DIMETHICONE; ISODODECANE; ALKYL (C12-15) BENZOATE; UNDECANE; TRIETHYLHEXANOIN; ISOHEXADECANE; NYLON-12; CAPRYLYL TRISILOXANE; BUTYLOCTYL SALICYLATE; PHENETHYL BENZOATE; STYRENE/ACRYLAMIDE COPOLYMER (500000 MW); SILICON DIOXIDE; TRIDECANE; DICAPRYLYL CARBONATE; DICAPRYLYL ETHER; TALC; DIMETHICONE/PEG-10/15 CROSSPOLYMER IN DIMETHICONE 6 (130000 CPS); ALUMINUM STEARATE; PENTYLENE GLYCOL; PEG-9 POLYDIMETHYLSILOXYETHYL DIMETHICONE; ALUMINUM OXIDE; POLYHYDROXYSTEARIC ACID (2300 MW); PHENOXYETHANOL; MAGNESIUM SULFATE, UNSPECIFIED FORM; CAPRYLYL GLYCOL; PEG-8 LAURATE; DISTEARDIMONIUM HECTORITE; TRIETHOXYCAPRYLYLSILANE; TOCOPHEROL; PROPYLENE CARBONATE; BENZOIC ACID; POLYETHYLENE GLYCOL 450

Drug Facts

Active ingredients

Titanium dioxide 6%

Zinc oxide 5%

Purpose

Sunscreen

Uses

- helps prevent sunburn

- if used as directed with other sun protection measures (see Directions), decreases the risk of skin cancer and early skin aging caused by the sun

Warnings

For external use only

Do not use

on damaged or broken skin

When using this product

keep out of eyes. Rinse with water to remove.

Stop use and ask a doctor if

rash occurs

Keep out of reach of children.

If swallowed, get medical help or contact a Poison Control Center right away.

Directions

● apply liberally 15 minutes before sun exposure

● reapply at least every 2 hours

● use a water resistant sunscreen if swimming or sweating

● Sun Protection Measures. Spending time in the sun increases your risk of skin cancer and early skin aging. To decrease this risk,

regularly use a sunscreen with a Broad Spectrum SPF value of 15 or higher and other sun protection measures including:

● limit time in the sun, especially from 10 a.m. – 2 p.m.

● wear long-sleeved shirts, pants, hats, and sunglasses

● children under 6 months of age: Ask a doctor

Other information

protect the product in this container from excessive heat and direct sun

Inactive ingredients

water, dimethicone, isododecane, c12-15 alkyl benzoate, undecane, triethylhexanoin, isohexadecane, nylon-12, caprylyl methicone, butyloctyl salicylate, phenehyl benzoate, styrene/acrylates copolymer, silica, tridecane, dicaprylyl carbonate, dicaprylyl ether, talc, dimethicone/peg-10/15 crosspolymer, aluminum stearate, pentylene glycol, PEG-9 polydimethylsiloxyethyl dimethicone, alumina, polyhydroxystearic acid, phenoxyethanol, magnesium sulfate, caprylyl glycol, PEG-8 laurate, disterardimonioum hectorite, triethoxycaprylylsilane, tocopherol, propylene carbonate, artemia extract, benzoic acid, PEG-9

Questions or comments?

Call 1-800-811-1660

Monday - Friday (9 a.m. - 5 p.m. CST)